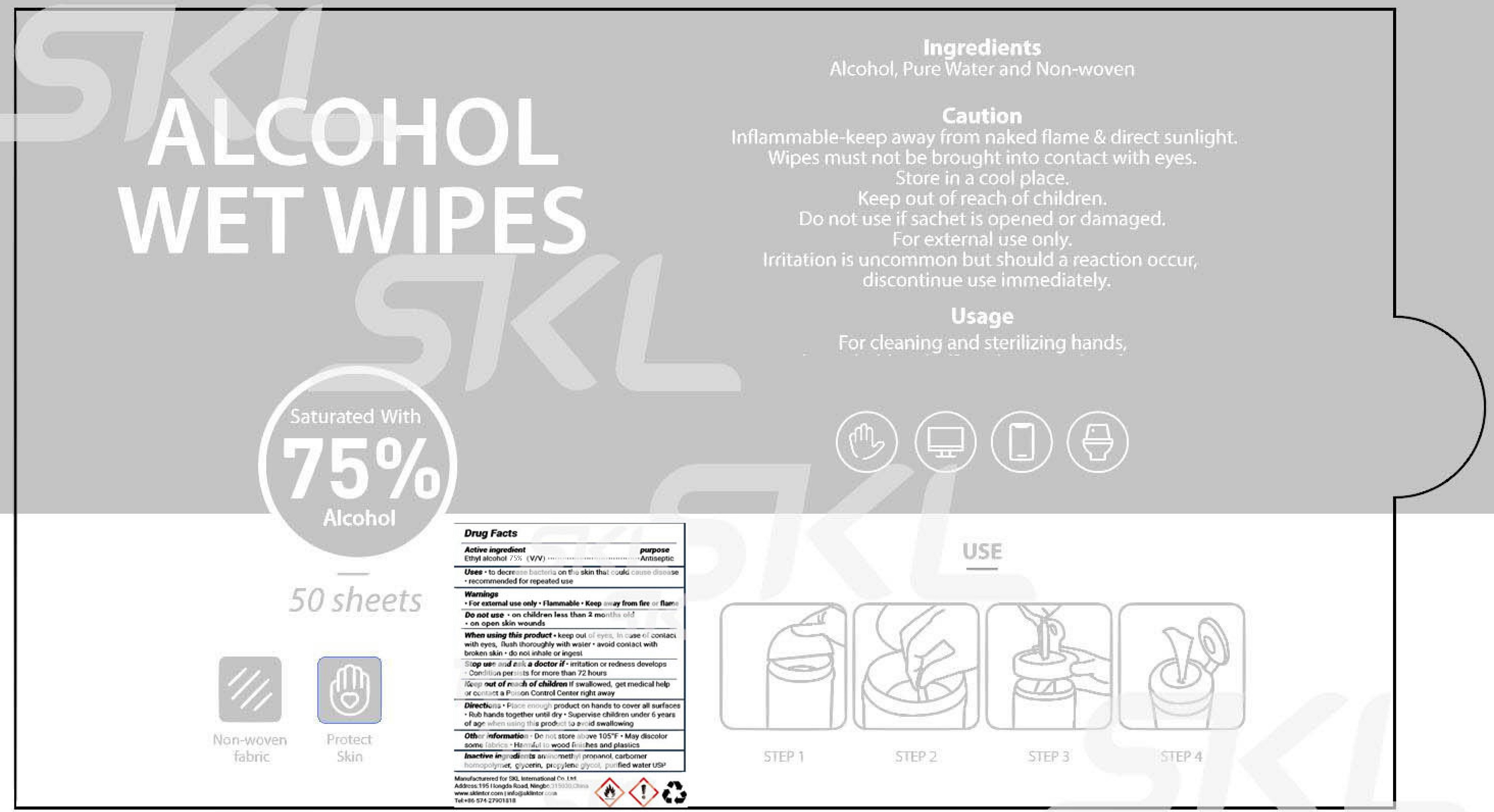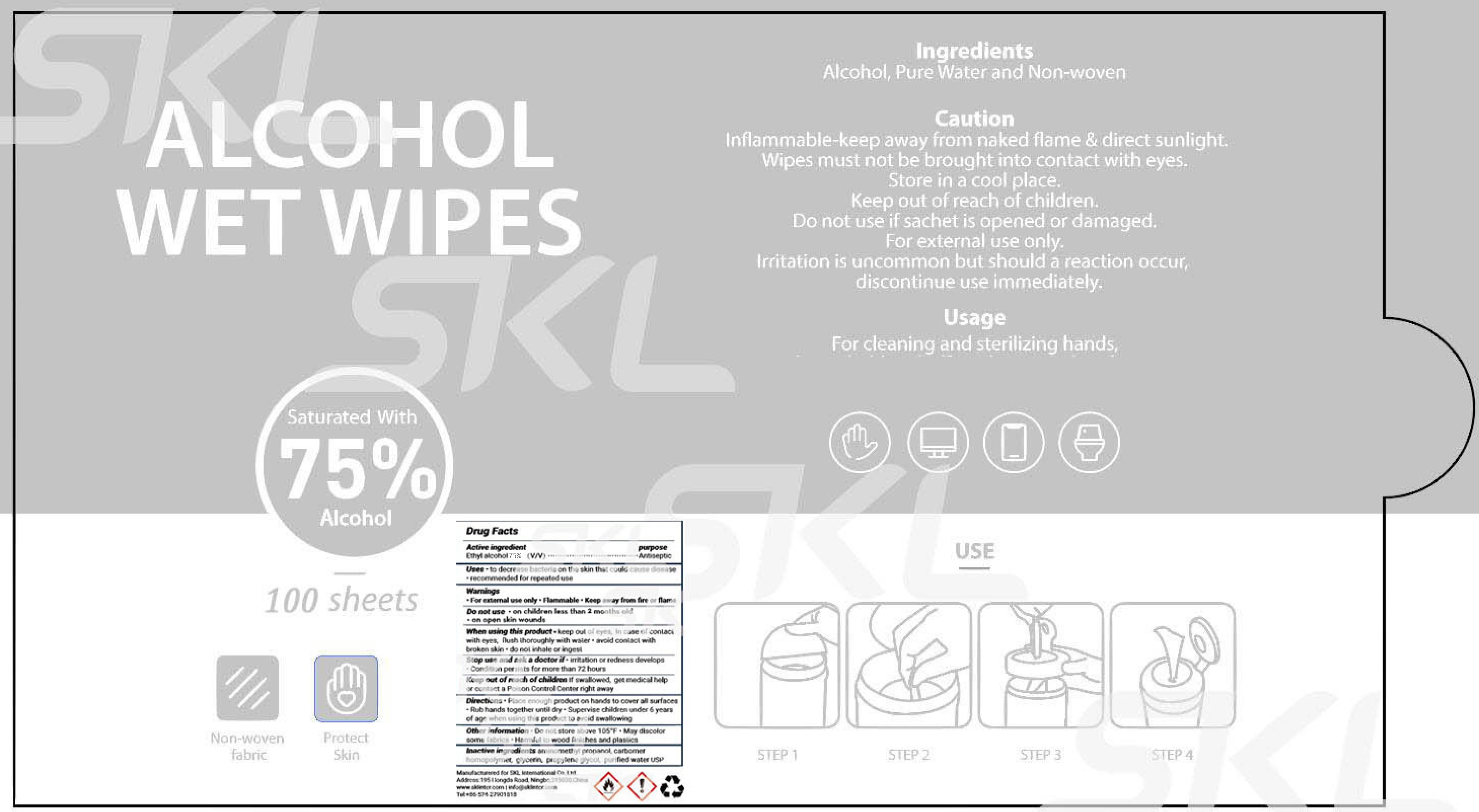 DRUG LABEL: Alcohol Wet Wipes
NDC: 74979-005 | Form: CLOTH
Manufacturer: Robert Gordon Ind. Ltd.
Category: otc | Type: HUMAN OTC DRUG LABEL
Date: 20200928

ACTIVE INGREDIENTS: ALCOHOL 0.75 mL/1 mL
INACTIVE INGREDIENTS: AMINOMETHYLPROPANOL; CARBOMER HOMOPOLYMER, UNSPECIFIED TYPE; GLYCERIN; PROPYLENE GLYCOL; WATER

Alcohol Wet Wipes

Active ingredient

Ethyl alcohol 75% (v/v)

Purpose

Antiseptic

Uses

- to decrease bacteria on the skin that could cause disease
- recommended for repeated use

Warnings

- For external use only
- Flammable
- Keep away from fire or flame

Do not use

- on children less than 2 months old
- on open skin wounds

When using this product

- keep out of eyes, ears, In case of contact with eyes, flush thoroughly with water.
- avoid contact with broken skin
- do not inhale or ingest

Stop use and ask a doctor if

- irritation or redness develops
- Condition persists for more than 72 hours

Keep out of reach of children.

If swallowed, get medical help or contact a Poison Control Center right away

Directions

- Place enough product on hands to cover all surfaces.
- Rub hands together until dry
- Supervise children under 6 years of age when using this product to avoid swallowing.

Other information

- Do not store above 105°F
- May discolor some fabrics
- Harmful to wood finishes and plastics

Inactive ingredients

aminomethyl propanol, carbomer homopolymer, glycerin, propylene glycol, purified water USP